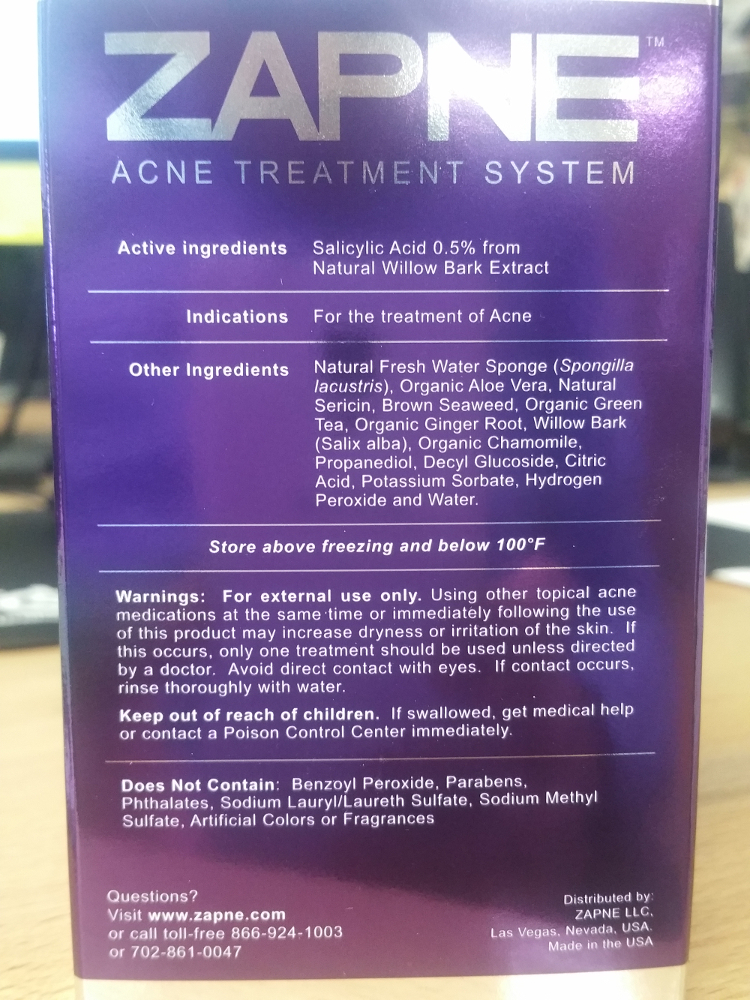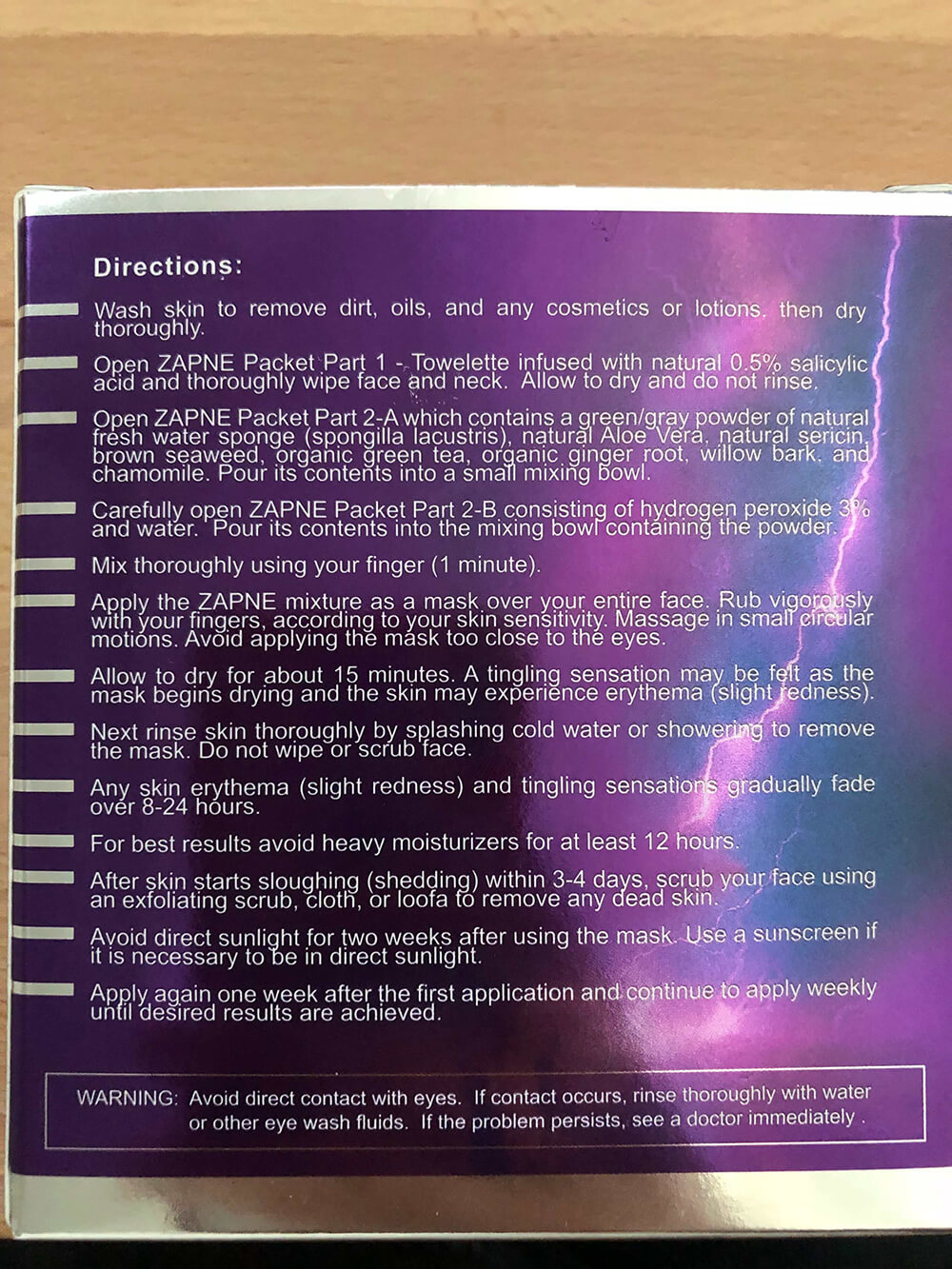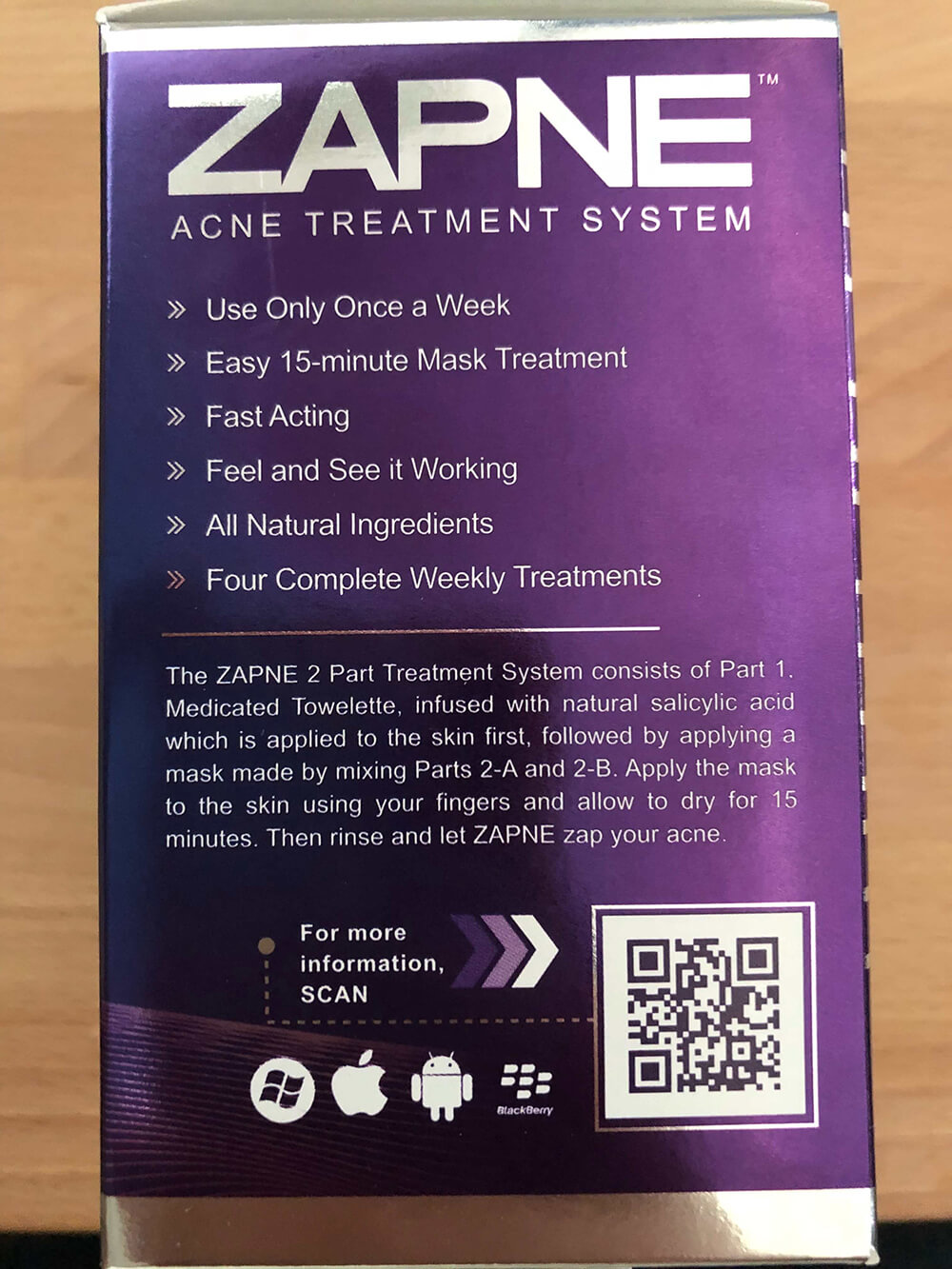 DRUG LABEL: Zapne
NDC: 71024-105 | Form: CLOTH
Manufacturer: Zapne LLC
Category: otc | Type: HUMAN OTC DRUG LABEL
Date: 20161004

ACTIVE INGREDIENTS: SALICYLIC ACID 20 mg/1300 mg
INACTIVE INGREDIENTS: SPONGILLA LACUSTRIS 1261 mg/1300 mg; SILK SERICIN 1.08 mg/1300 mg; NORI 1.08 mg/1300 mg; GREEN TEA LEAF 1.08 mg/1300 mg; GINGER 1.08 mg/1300 mg; WILLOW BARK 1.08 mg/1300 mg; CHAMOMILE 1.08 mg/1300 mg; ALOE VERA LEAF 325 mg/1300 mg

ZAPNE PRODUCT OTC DRUG LABEL

Directions:

- Wash skin to remove dirt, oils, and any cosmetics or lotions, then dry thoroughly.
- Open ZAPNE Packet Part 1 - Towelette infused with natrual 0.5% salicylic acid and thoroughly wipe face and neck. Allow to dry and do not rinse.
- Open Zapne Packet part 2-A which contains a green/gray powder of natrual fresh water sponge (spongilla lacustris), natural Aloe Vera, natrual sericin, brown seaweed, organic green tea, organic ginger root, willow bark, and chamomile. Pour its contens into a small mixing bowl.
- Carefully open ZAPNE Packet Part 2-B consisting of hydrogen peroxide 3% and water. Pour its content into a mixing bowl containing the powder.
- Mix thoroughly using your finger (1 minute).
- Apply the ZAPNE mixture as a max over your entire face. Rub vigorously with your fingers, according to your skin sensitivity. Massage in small circular motions. Avoid applying the mask too close to the eyes.
- Allow to drive for about 15 minutes. A tingling sensation may be felt as the mask begins drying and the skin may experience erythema (slight redness),
- Next rinse skin thoroughly by splashing cold water or showering to remove the mask. Do not wipe or scrub face.
- Any skin erythema (slight redness) and tingling sensations gradually fade over 8-24 hours.
- For best results avoid heavy moisturizers for at least 12 hours .
- After skin starts sloughing (shedding) within 3-4 days, scrub your face using an exfoliating scrub, cloth, or loofa to remove any dead skin.
- Avoid direct sunlight for two weeks after using the mask. Use a sunscreen if it is necessary to be in direct sunlight.
- Apply again one week after the first application and contine to apply weekly until the desired results are acheived.

WARNING: Avoid direct contact with eyes. If contact occurs, rinse thoroughly with water or other eye wash fuilds. If the problem persists, see a doctor immediately.

Warnings: For external use only.

Using other topical acne medications at the same time or immediately following the use of this product may increase dryness or irritation of the skin. If this occurs, only one treatment should be used unless directed by a doctor. Avoid direct contact with eyes. If contact occurs, rinse thoroughly with water.

Keepy out of reach of children. If swallowed, get medical help or contact a Poison Control Center immediately.

INACTIVE INGREDIENT

Other Ingredients

Natural Fresh Water Sponge(spongilla

lacustris), organic Aloe Vera, Natural

Sericin, Brown Seaweed, Organic Green

Tea, Organic Ginger Root, Willow Bark

(Salix alba), Organic Chamomile,

Propanediol, Decyl Glucoside, Citric

Acid, Potassium Sorbate, Hydrogen

Peroxide and Water

Indications: For the treatment of Acne

Keep out of reach of children: If swallowed, get medical help or contact a Poison Control Center immediately.

PURPOSE

Zapne

Acne Treatment System

- Use Only Once a Week
- Easy 15-minute Mask Treatment
- Fast Acting
- Feel and See it Working
- All NAtrual Ingredients
- Four Complete Weekly Treatments

ACTIVE INGREDIENT

Active ingredients: salicylic acid 0.5% from natural willow bark extract

PACKAGE LABEL

active ingredients | salicylic acid 0.5% from; natural willow bark extract
Indications | For the treatment of Acne
Other Ingredients | Natural Fresh Water Sponge(spongilla; lacustris), organic Aloe Vera, Natural; Sericin, Brown Seaweed, Organic Green; Tea, Organic Ginger Root, Willow Bark; (Salix alba), Organic Chamomile,; Propanediol, Decyl Glucoside, Citric; Acid, Potassium Sorbate, Hydrogen; Peroxide and Water

Store above freezing and below 100 F

Warnings: For external use only. Using other topical acne

medications at the same time or immediately following the use

of this product may increase dryness or irritation of the skin. If

this occurs, only one treatment should be used unless directed

by a doctor. avoid direct contact with eyes. If contact occurs,

rinse thoroughly with water.

Keep out of reach of children. If swallowed, get medical help

or contact a Poison Control Center immediately.

Does Not Contain: Benzoyl Peroxide, Parabens,

Phthalates, Sodium Lauryl/Laureth Sulfare, Sodium Methyl

Sulface, Artificial Colors or Fragrances